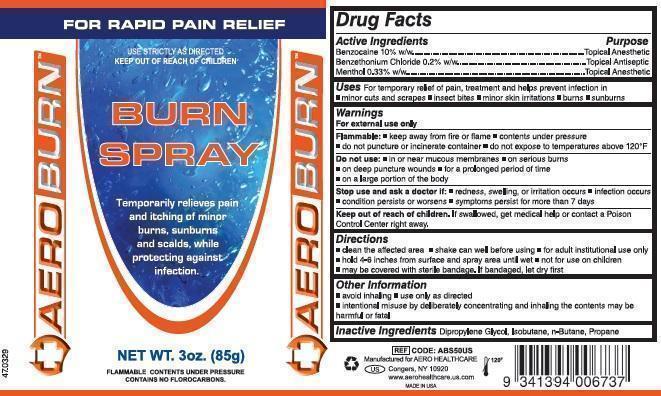 DRUG LABEL: Aeroburn Burn First Aid
NDC: 55305-116 | Form: AEROSOL, SPRAY
Manufacturer: Aero Healthcare, LLC.
Category: otc | Type: HUMAN OTC DRUG LABEL
Date: 20140924

ACTIVE INGREDIENTS: BENZETHONIUM CHLORIDE 170 mg/85 g; BENZOCAINE 8500 mg/85 g; MENTHOL 281 mg/85 g
INACTIVE INGREDIENTS: DIPROPYLENE GLYCOL; ISOBUTANE; BUTANE; PROPANE

AEROBURN BURN SPRAY

Active Ingredients

Benzocaine 10% w/w
Benzethonium Chloride .2% w/w
Menthol .33% w/w

Purpose

Topical Anesthetic
Topical Antiseptic
Topical Anesthetic

Uses

For temporary relief of pain, treatment and helps prevent infection in

- minor cuts and scrapes
- insect bites
- minor skin irritations
- burns
- sunburns

Warnings

For external use only

Flammable

- keep away from fire or flame
- contents under pressure
- do not puncture or incinerate container
- do not expose to temperatures above 120°F

Do not use

- in or near mucous membranes
- on serious burns
- on deep puncture wounds
- for prolonged period of time
- on a large portion of the body

Stop use and ask a doctor if

- redness, swelling, or irritation occurs
- infection occurs
- condition persists or worsens
- symptoms persist for more than 7 days

Keep out of reach of children.

If swallowed, get medical help or contact a Poison Control Center right away.

Directions

- clean the affected area
- shake can well before using
- for adult institutional use only
- hold 4-6 inches from surface and spray area until wet
- not for use on children
- may be covered with a sertile bandage. If bandaged, let dry first.

Other information

- avoid inhaling
- use only as directed
- intentional misuse by deliberately concentrating and inhaling the contents may be harmful or fatal

Inactive Ingredients

Dipropylene Glycol, Isobutane, n-Butane, Propane